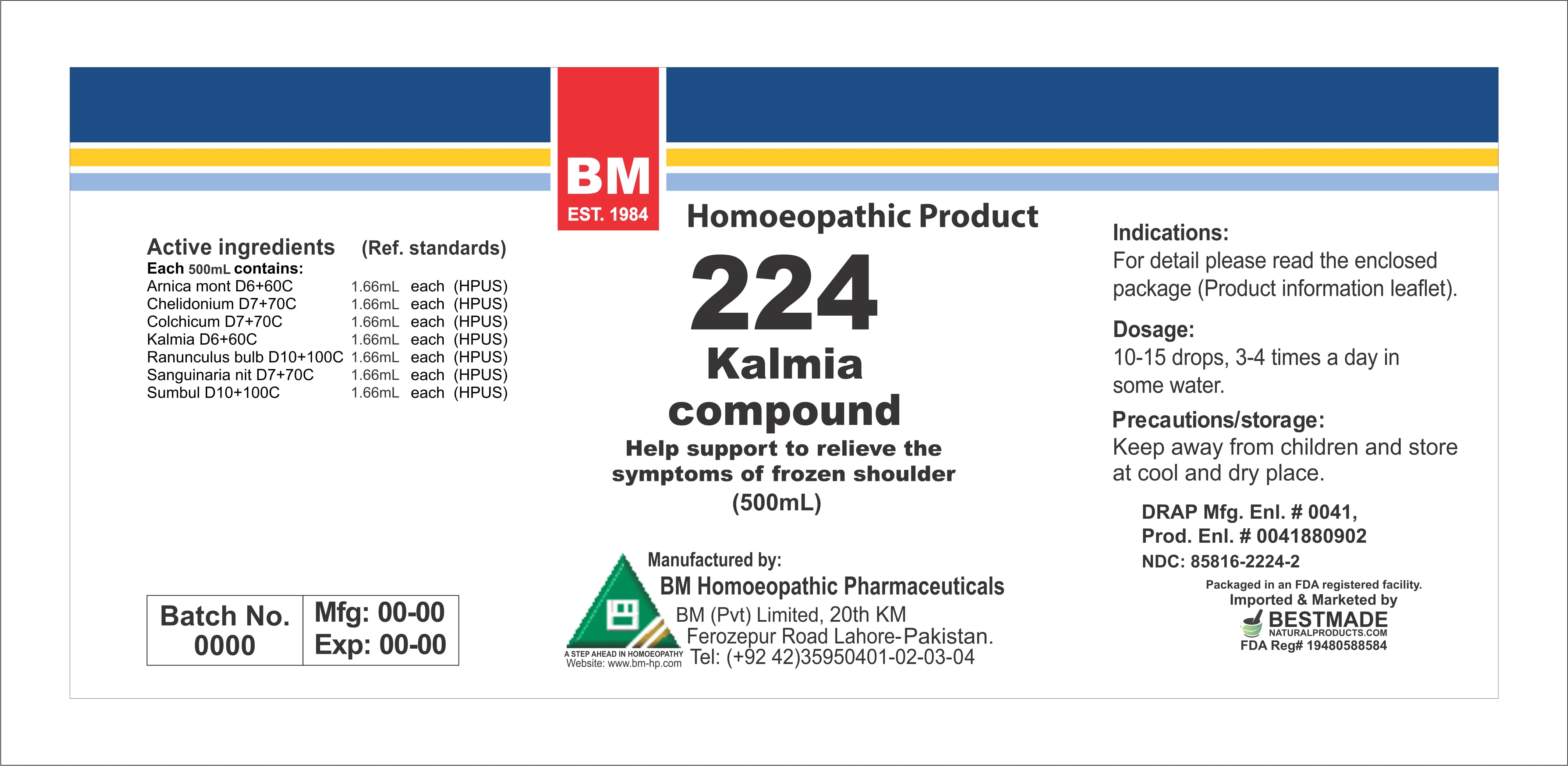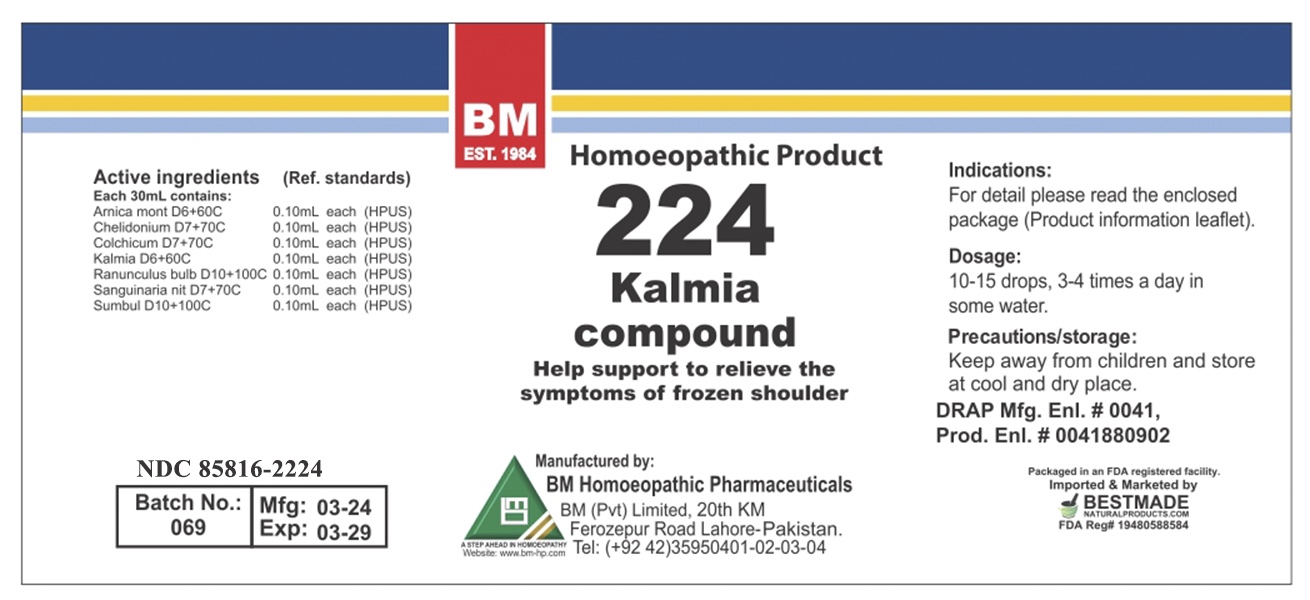 DRUG LABEL: KALMIA
NDC: 85816-2224 | Form: LIQUID
Manufacturer: BM Private Limited
Category: homeopathic | Type: HUMAN OTC DRUG LABEL
Date: 20260215

ACTIVE INGREDIENTS: FERULA SUMBUL ROOT 10 [hp_X]/1 mL; RANUNCULUS BULBOSUS ROOT 10 [hp_X]/1 mL; SANGUINARIA CANADENSIS ROOT 7 [hp_X]/1 mL; CHELIDONIUM MAJUS 7 [hp_X]/1 mL; COLCHICUM AUTUMNALE BULB 7 [hp_X]/1 mL; ARNICA MONTANA 6 [hp_X]/1 mL; KALMIA LATIFOLIA LEAF 6 [hp_X]/1 mL
INACTIVE INGREDIENTS: ALCOHOL 0.96 mL/1 mL

HOMEOPATHIC LIQUID KALMIA/ BM224

DOSAGE AND ADMINISTRATION

10-15 drops, 3-4 times a day in some water

ACTIVE INGREDIENT

arnica montana, chelidonium, colchicum, kalmia, ranunculus bulb, sanguinaria nit, sumbul

INACTIVE INGREDIENT

ALCOHOL

INDICATIONS AND USAGE

For detail, please read the enclosed package (product information leaflet)

PURPOSE

For detail, please read the enclosed package (product information leaflet)

KEEP OUT OF REACH OF CHILDREN

Precautions/storage:
Keep away from children and store at cool and dry place.

WARNINGS

Precautions/storage:
Keep away from children and store at cool and dry place.

Package 1 Package 2